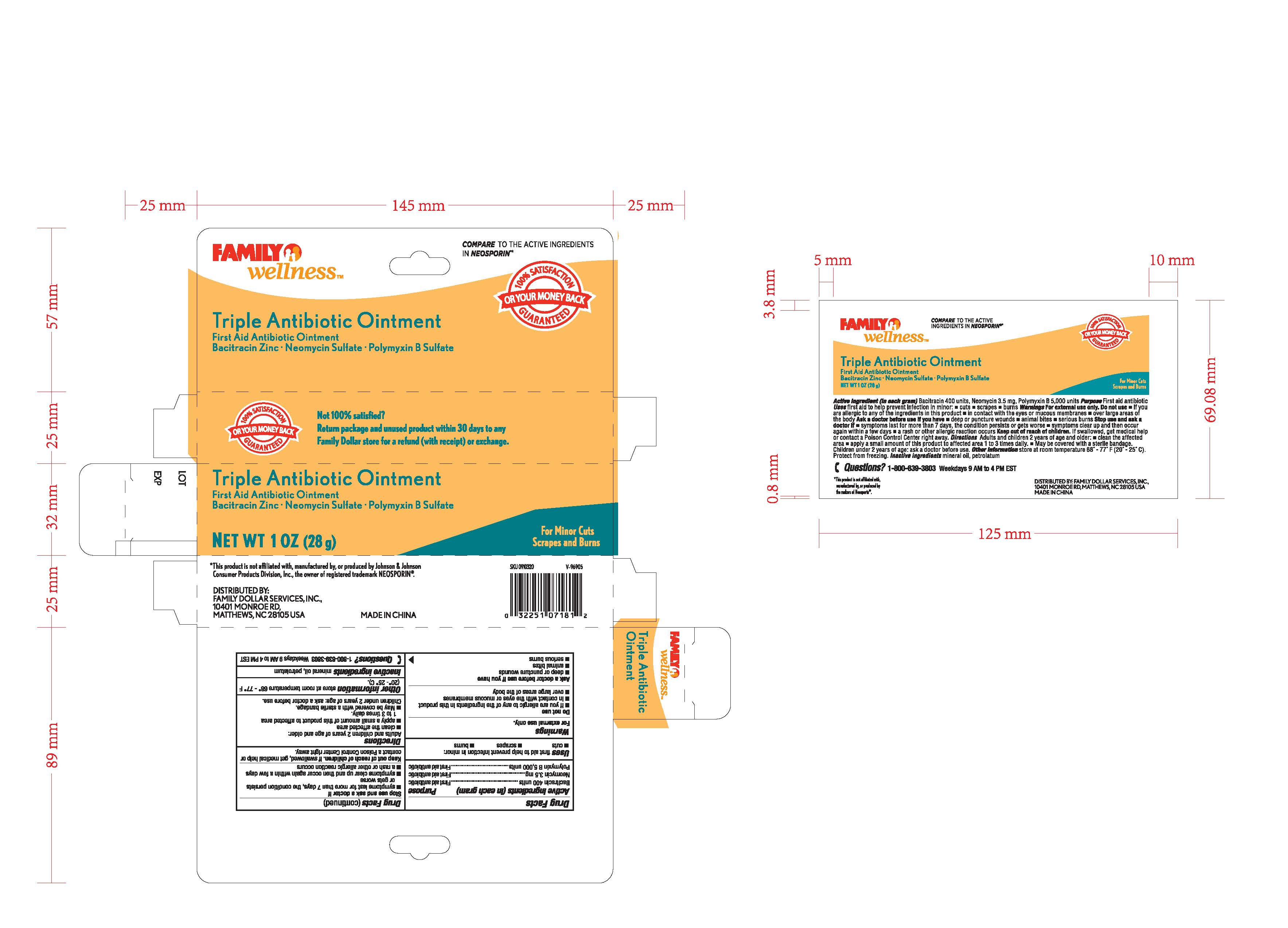 DRUG LABEL: Family wellness
NDC: 69571-003 | Form: OINTMENT
Manufacturer: FRONT PHARMACEUTICAL PLC
Category: otc | Type: HUMAN OTC DRUG LABEL
Date: 20231027

ACTIVE INGREDIENTS: BACITRACIN ZINC 0.41 g/100 g; NEOMYCIN SULFATE 0.0035 g/100 g; POLYMYXIN B SULFATE 0.52 g/100 g
INACTIVE INGREDIENTS: MINERAL OIL; PETROLATUM

Active ingredients (in each gram)

Bacitracin 400 units

Neomycin 3.5 mg

Polymyxin B 5,000 units

Purpose

First aid antibiotic

First aid antibiotic

First aid antibiotic

INDICATIONS AND USAGE

first aid to help prevent infection in minor: Uses

-uses -scrapes -burns

Warnings

. For external use only

Do not use

Ask a doctor before use if you have

Stop use and ask a doctor if

- if you are allergic to any of the ingredients in this product
- in contact with the eyes or mucous membranes
- over large areas of the body

- deep or puncture wounds
- animal bites
- serious burns

- symptoms persist for mroe than 7 days, the condition persists or gets worse
- symptoms clear up and then occur again within a few days
- a rash or other allergic reaction occurs

KEEP OUT OF REACH OF CHILDREN

. If swallowed, get medical help or Keep out of reach of children

contact a Poison Control Center right away.

Directions

Adults and children 2 years of age and older:

Children under 2 years of age: ask a doctor before use.

- clean the affected area
- apply a small amount of this product to affected area 1 to 3 times daily
- May be covered with a sterile bandage.

STORAGE AND HANDLING

store at room temperature 68 - 77 F Other information

(20-25 C).

QUESTIONS

1-800-639-3803 Weekdays 9 AM to 4 PM EST Questions?

mineral oil, petrolatum Inactive ingredients